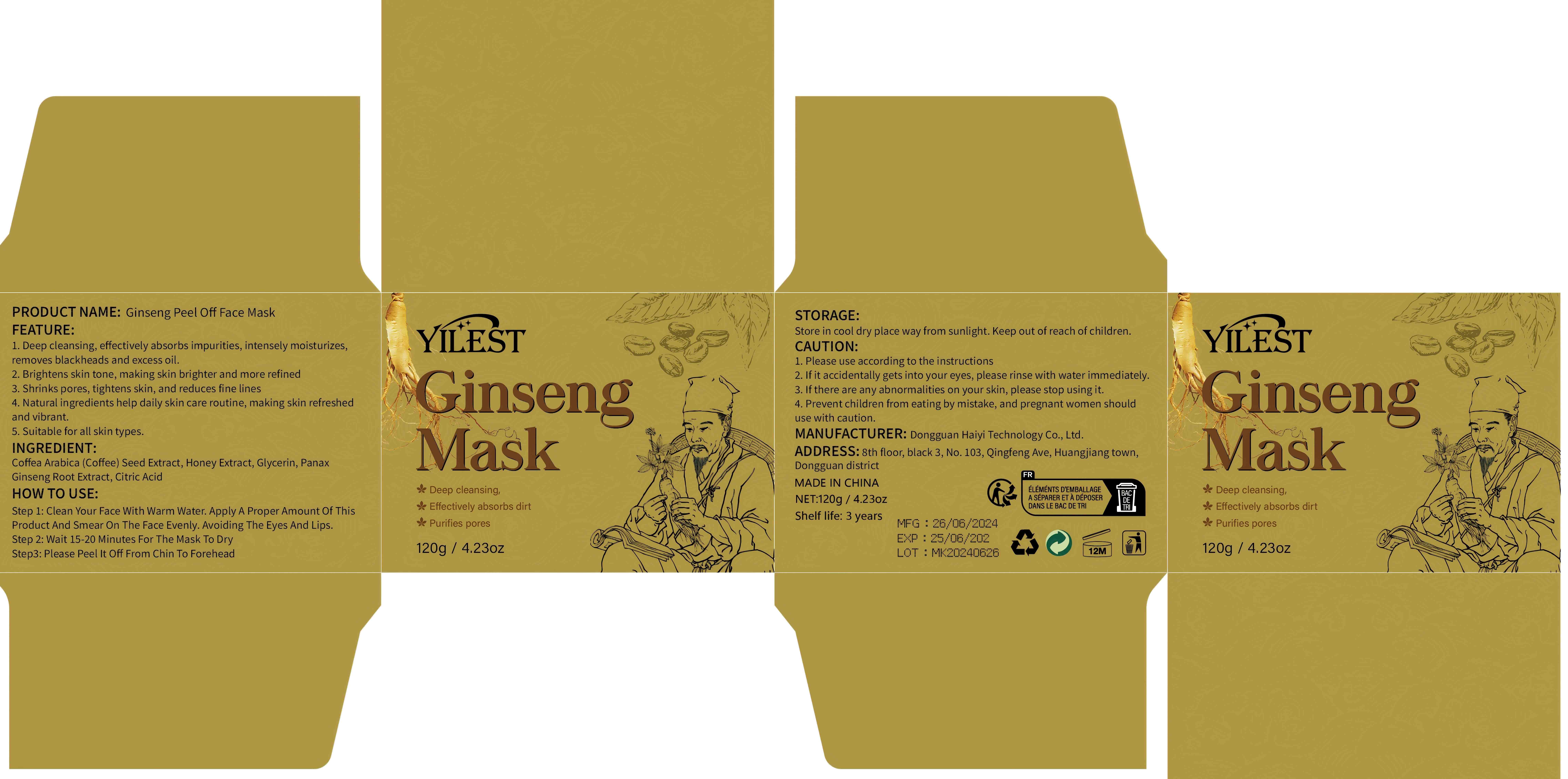 DRUG LABEL: Ginseng Peel Off Face Mask
NDC: 84732-059 | Form: PASTE
Manufacturer: Dongguan Haiyi Technology Co.,Ltd.
Category: otc | Type: HUMAN OTC DRUG LABEL
Date: 20241022

ACTIVE INGREDIENTS: COFFEA ARABICA (COFFEE) SEED EXTRACT 1 mg/120 g
INACTIVE INGREDIENTS: CITRIC ACID; ASIAN GINSENG; HONEY EXTRACT; GLYCERIN

Active ingredient

Coffea Arabica (Coffee) Seed Extract

Inactive ingredient

Honey Extract, Glycerin, Panax Ginseng Root Extract, Citric Acid

Purpose section

1. Deep cleansing, effectively absorbs impurities, intensely moisturizes.removes blackheads and excess oil.

2. Brightens skin tone, making skin brighter and more refined

3. Shrinks pores, tightens skin, and reduces fine lines

4. Natural ingredients help daily skin care routine, making skin refreshedand vibrant.
5. Suitable for all skin types.

Warning

1. Please use accordingto the instructions
2. lf it accidentally gets into your eyes, please rinse with waterimmediately.

3. lf there are any abnormalities on your skin, please stop using it.

4. Prevent children from eating by mistake, and pregnant women shoulduse with caution.

stop use

This product may cause allergic reactions in asmall number of people.
lf youexperience any discomfort,please stop using it immediately.

not use

Not suitable for use by children, pregnantor breast feeding people.

OUT OF CHILDREN

KEEP THE PRODUCT OUT OF REACH OF CHILDREN to

HOW TO USE

Step 1: Clean Your Face With Warm Water. Apply A Proper Amount Of ThisProduct And Smear On The Face Evenly. Avoiding The Eyes And Lips.

Step 2: Wait 15-20 Minutes For The Mask To Dry

Step3: Please Peel lt Off From Chin To Forehead

Dosage

take an appropriateamount,Use 2-3 times a week